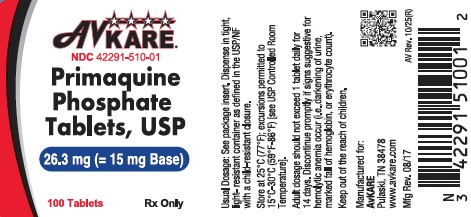 DRUG LABEL: PRIMAQUINE PHOSPHATE
NDC: 42291-510 | Form: TABLET, FILM COATED
Manufacturer: AvKARE
Category: prescription | Type: HUMAN PRESCRIPTION DRUG LABEL
Date: 20260225

ACTIVE INGREDIENTS: PRIMAQUINE PHOSPHATE 15 mg/1 1
INACTIVE INGREDIENTS: LACTOSE MONOHYDRATE; CELLULOSE, MICROCRYSTALLINE; STARCH, PREGELATINIZED CORN; TALC; MAGNESIUM STEARATE; HYPROMELLOSE 2910 (15 MPA.S); FD&C YELLOW NO. 6; TITANIUM DIOXIDE; TRIACETIN

PRIMAQUINE PHOSPHATE TABLETS, USP

DESCRIPTION

Primaquine phosphate is 8-[(4-Amino-1-methylbutyl)-amino]-6- methoxyquinoline phosphate, a synthetic compound with potent antimalarial activity. Each tablet contains 26.3 mg of primaquine phosphate (equivalent to 15 mg of primaquine base). The dosage is customarily expressed in terms of the base.

Inactive Ingredients: Hypromellose, Lactose Monohydrate, Magnesium Stearate, Microcrystalline Cellulose, Triacetin, Pregelatinized Starch, FD&C Yellow#6/Sunset Yellow FCF Aluminum Lake, Talc, Titanium Dioxide.

CLINICAL PHARMACOLOGY

Primaquine phosphate is an 8-amino-quinoline compound which eliminates tissue (exoerythrocytic) infection. Thereby, it prevents the development of the blood (erythrocytic) forms of the parasite which are responsible for relapses in vivax malaria. Primaquine phosphate is also active against gametocytes of Plasmodium falciparum.

INDICATIONS AND USAGE

Primaquine phosphate is indicated for the radical cure (prevention of relapse) of vivax malaria.

CONTRAINDICATIONS

Severe glucose-6-phosphate dehydrogenase (G6PD) deficiency (see WARNINGS).

Pregnant women (see WARNINGS, Usage in Pregnancy).

Primaquine phosphate is contraindicated in acutely ill patients suffering from systemic disease manifested by tendency to granulocytopenia, such as rheumatoid arthritis and lupus erythematosus. The drug is also contraindicated in patients receiving concurrently other potentially hemolytic drugs or depressants of myeloid elements of the bone marrow.

Because quinacrine hydrochloride appears to potentiate the toxicity of antimalarial compounds which are structurally related to primaquine, the use of quinacrine in patients receiving primaquine is contraindicated. Similarly, primaquine should not be administered to patients who have received quinacrine recently, as toxicity is increased.

WARNINGS

Hemolytic anemia and G6PD deficiency

Due to the risk of hemolytic anemia in patients with G6PD deficiency, G6PD testing has to be performed before using primaquine. Due to the limitations of G6PD tests, physicians need to be aware of residual risk of hemolysis and adequate medical support and follow-up to manage hemolytic risk should be available.

Primaquine should not be prescribed for patients with severe G6PD deficiency (see CONTRAINDICATIONS).

In case of mild to moderate G6PD deficiency, a decision to prescribe primaquine must be based on an assessment of the risks and benefits of using primaquine. If primaquine administration is considered, baseline hematocrit and hemoglobin must be checked before treatment and close hematological monitoring (e.g. at day 3 and 8) is required. Adequate medical support to manage hemolytic risk should be available.

When the G6PD status is unknown and G6PD testing is not available, a decision to prescribe primaquine must be based on an assessment of the risks and benefits of using primaquine. Risk factors for G6PD deficiency or favism must be assessed. Baseline hematocrit and hemoglobin must be checked before treatment and close hematological monitoring (e.g. at day 3 and 8) is required. Adequate medical support to manage hemolytic risk should be available.

Discontinue the use of primaquine phosphate promptly if signs suggestive of hemolytic anemia occur (darkening of the urine, marked fall of hemoglobin or erythrocytic count).

Hemolytic reactions (moderate to severe) may occur in individuals with G6PD deficiency and in individuals with a family or personal history of favism. Areas of high prevalence of G6PD deficiency are Africa, Southern Europe, Mediterranean region, Middle East, South-East Asia, and Oceania. People from these regions have a greater tendency to develop hemolytic anemia (due to a congenital deficiency of erythrocytic G6PD) while receiving primaquine and related drugs.

Usage in Pregnancy

Safe usage of this preparation in pregnancy has not been established. Primaquine is contraindicated in pregnant women. Even if a pregnant woman is G6PD normal, the fetus may not be (see CONTRAINDICATIONS). Animal data show toxicity to reproduction.

Nonclinical data from studies conducted in bacteria and in animals treated with primaquine show evidence of gene mutations and chromosomal/DNA damage, teratogenicity, and injury to embryos and developing fetuses when primaquine is administered to pregnant animals. Patients must be informed of the potential for adverse genetic and reproductive effects associated with Primaquine treatment (See PRECAUTIONS, Carcinogenesis, Mutagenesis, and Impairment of fertility, and Animal Pharmacology and /or Animal Toxicology).

Use in Females and Males of Reproductive Potential

Pregnancy Testing

Sexually-active females of reproductive potential should have a pregnancy test prior to starting treatment with Primaquine.

Contraception

Patients should avoid pregnancy during treatment. The use of effective contraception is recommended during treatment and after the end of treatment as follows: Advise sexually-active females of child bearing potential to use effective contraception (methods that result in less than 1% pregnancy rates) when using Primaquine and after stopping treatment until completion of an on-going ovulatory cycle (e.g., up to next menses). Advise treated males whose partners may become pregnant, to use a condom while on treatment and for 3 months after stopping treatment with Primaquine.

Lactation

It is not known whether primaquine is excreted in human milk. Because many drugs are excreted in human milk and because of the potential for serious adverse reactions in nursing infants from primaquine, a decision should be made whether to discontinue nursing or to discontinue the drug, taking into account the importance of the drug to the mother.

PRECAUTIONS

Blood Monitoring

Since anemia, methemoglobinemia, and leukopenia have been observed following administration of large doses of primaquine, the adult dosage of 1 tablet (= 15 mg base) daily for fourteen days should not be exceeded. In G6PD normal patients it is also advisable to perform routine blood examinations (particularly blood cell counts and hemoglobin determinations) during therapy.

If primaquine phosphate is prescribed for an individual who has shown a previous idiosyncratic reaction to primaquine phosphate as manifested by hemolytic anemia, methemoglobinemia, or leukopenia; an individual with a family or personal history of hemolytic anemia or nicotinamide adenine dinucleotide (NADH) methemoglobin reductase deficiency, the person should be observed closely. In all patients, the drug should be discontinued immediately if marked darkening of the urine or sudden decrease in hemoglobin concentration or leukocyte count occurs.

Potential Prolongation of QT Interval

Due to potential for QT interval prolongation, monitor ECG when using primaquine in patients with cardiac disease, long QT syndrome, a history of ventricular arrhythmias, uncorrected hypokalemia and/or hypomagnesemia, or bradycardia (<50 bpm), and during concomitant administration with QT interval prolonging agents (see PRECAUTIONS, Drug Interactions, ADVERSE REACTIONS, and OVERDOSAGE).

Carcinogenesis, Mutagenesis, Impairment of fertility

No carcinogenicity studies have been conducted with Primaquine. No fertility studies have been conducted with Primaquine. Primaquine is reported in the literature to be a weak genotoxic agent which elicits both gene mutations^1, chromosomal damage and DNA strand breaks^2. The publications reported positive results in the in vitro reverse gene mutation assays using bacteria (Ames test)^(3 4) and in the in vivo studies using rodents (mouse bone marrow cell sister chromatid exchange, mouse bone marrow cell chromosome abnormality, and rat DNA strand-breaks in multiple organs)^(2 5)· The genotoxicity data obtained in vitro and in rodent models are suggestive of a human risk for genotoxicity with primaquine administration (see WARNINGS, Usage in Pregnancy).

Animal Pharmacology and /or Animal Toxicology

Literature data on reproductive toxicology identified embryo-fetal development toxicity. In studies in rats, teratogenic effects on fetus were observed (see WARNINGS, Usage in Pregnancy).

In the first reproductive toxicity study^6, primaquine was administered orally to rats between gestation day (GD) 6 and GD15 at dose-levels of 10.3, 30.8 and 61.5 mg/kg/day (as base) (representing approximatively 7, 20 and 40 times the human dose (HD) (on a body surface area comparison) when considering a human body weight of 60 kg). High dose-levels induced death of pregnant females in almost all cases, while lower dose-levels caused maternal toxicity. At cesarean section, embryo resorption, a decrease in fetal survival rate and body size, internal abnormalities (including hydrocephalia, heterotaxia), and an increase in skeletal variations were observed at the mid dose-level. There were no fetal abnormalities at the low dose-level providing a potential safety margin of at least 7 times the recommended clinical dose.

For the second reproductive toxicity study^7, 6 to 10 animals per group were used. Dose-levels of 0.57, 5.7, 11.4 and 34 mg/kg/day of primaquine (as base) (representing approximatively 0.4, 4, 7 and 22 times the HD (on a body surface area comparison) were administered orally to Sprague Dawley rats between GD8 and GD16, or of 57 mg/kg only once on GD13 (representing more than 37 times the HD on a body surface area comparison). A total of 1/7 and 4/6 pregnant females at 34 mg/kg/day and at 57 mg/kg, respectively, died. Primaquine-associated teratogenic malformations (including cleft palate and small chin) were observed in 4/54 fetuses in the 57 mg/kg single-dose group.

Drug Interactions

Caution is advised if primaquine is used concomitantly with other drugs that prolong the QT interval (see PRECAUTIONS, ADVERSE REACTIONS, and OVERDOSAGE).

Geriatric Use

Clinical studies of primaquine did not include sufficient numbers of subjects aged 65 and over to determine whether they respond differently from younger subjects. Other reported clinical experience has not identified differences in responses between the elderly and younger patients. In general, dose selection for an elderly patient should be cautious, usually starting at the low end of the dosing range, reflecting the greater frequency of decreased hepatic, renal, or cardiac function, and of concomitant disease or other drug therapy.

ADVERSE REACTIONS

To report SUSPECTED ADVERSE REACTIONS, please call AvKARE at 1-855-361-3993 or FDA at 1-800-FDA-1088 or www.fda.gov/medwatch

Gastrointestinal: Nausea, vomiting, epigastric distress, and abdominal cramps.

Hematologic: Leukopenia, hemolytic anemia in G6PD deficient individuals, and methemoglobinemia in nicotinamide adenine dinucleotide (NADH) methemoglobin reductase deficient individuals.

Cardiac: Cardiac arrhythmia and QT interval prolongation (see PRECAUTIONS, OVERDOSAGE).

Nervous System: Dizziness.

Skin and Soft Tissue: Rash, pruritus.

OVERDOSAGE

Symptoms of overdosage of primaquine phosphate include abdominal cramps, vomiting, burning epigastric distress, central nervous system and cardiovascular disturbances, including cardiac arrhythmia and QT interval prolongation, cyanosis, methemoglobinemia, moderate leukocytosis or leukopenia, and anemia. The most striking symptoms are granulocytopenia and acute hemolytic anemia in G6PD deficient patients. Acute hemolysis occurs, but patients recover completely if the dosage is discontinued.

DOSAGE AND ADMINISTRATION

Primaquine phosphate is recommended only for the radical cure of vivax malaria, the prevention of relapse in vivax malaria, or following the termination of chloroquine phosphate suppressive therapy in an area where vivax malaria is endemic. Patients suffering from an attack of vivax malaria or having parasitized red blood cells should receive a course of chloroquine phosphate, which quickly destroys the erythrocytic parasites and terminates the paroxysm. Primaquine phosphate should be administered concurrently in order to eradicate the exoerythrocytic parasites in a dosage of 1 tablet (equivalent to 15 mg base) daily for 14 days.

HOW SUPPLIED

Primaquine Phosphate Tablets, USP are supplied as orange colored, round, biconvex, film-coated tablets of 26.3 mg (= 15 mg base), debossed with a "059" on one side and plain on the other side.

Available in bottles of 100 (NDC 42291-510-01)

Store at 25° C (77° F); excursions permitted to 15° C – 30° C (59° F – 86° F) [see USP Controlled Room Temperature]

Dispense in tight, light-resistant container as defined in the USP/NF.

CLINICAL STUDIES

Persons with acute attacks of vivax malaria, provoked by the release of erythrocytic forms of the parasite, respond readily to therapy, particularly to chloroquine phosphate. Primaquine eliminate tissue (exoerythrocytic) infection and prevents relapses in experimentally induced vivax malaria in human volunteers and in persons with naturally occurring infections and is a valuable adjunct to conventional therapy in vivax malaria.

REFERENCES

1. Shubber EK, Jacobson-Kram D, Williams JR. Comparison of the Ames assay and the induction of sister chromatid exchanges: results with ten pharmaceuticals and five selected agents. Cell Biol Toxicol.1986; 2:379-99.
2. Chatterjee T, Muhkopadhyay A, Khan KA, Giri AK. Comparative mutagenic and genotoxic effects of three antimalarial drugs, chloroquine, primaquine and amodiaquine. Mutagenesis. 1998;13:619-24.
3. Marss TC. Bright JE, Morris BC. Methemoglobinogenic potential of primaquine and its mutagenicity in the Ames test. Toxicol Lett. 1987; 36:281-7.
4. Ono T, Norimatsu M, Yoshimura H. Mutagenic evaluation of primaquine, pentaquine and pamaquine in the Salmonella/mammalian microsome assay. Mutat Res. 1994; 325:7-10.
5. Giovanella F, Ferreira GK, de Prá1 SDT, Carvalho-SilvaM, GomesLM, Scaini G, Goncalves RC4, Michels M, Galant LS, Longaretti LM, Dajori AL, AndradeVM, DalPizzol F, Streck EL, de Souza RP. Effects of primaquine and chloroquine on oxidative stress parameters in rats. Anais da Academia Brasileira de Ciencias (Annals of the Brazilian Academy of Sciences). 2015; 87: 1487-1496.
6. Trutter JA, Reno FE, Durloo RS. Teratogenicity studies wrth a candidate antileishmanial drug. The Toxicologist. 1983; 3:65.
7. Beveridge E, Caldwell IC, Latter VS, Neal RA, Udall V, Waldron MM. The activity against Trypanosoma cruzi and cutaneous leishmaniasis, and toxicity, of moxipraquine (349C59). Trans R Soc Trop Med Hyg. 1980; 74:43-51.

Rx Only

Manufactured for:
AvKARE
Pulaski, TN 38478
Mfg. Rev. 01/18
AV Rev. 08/25(M)